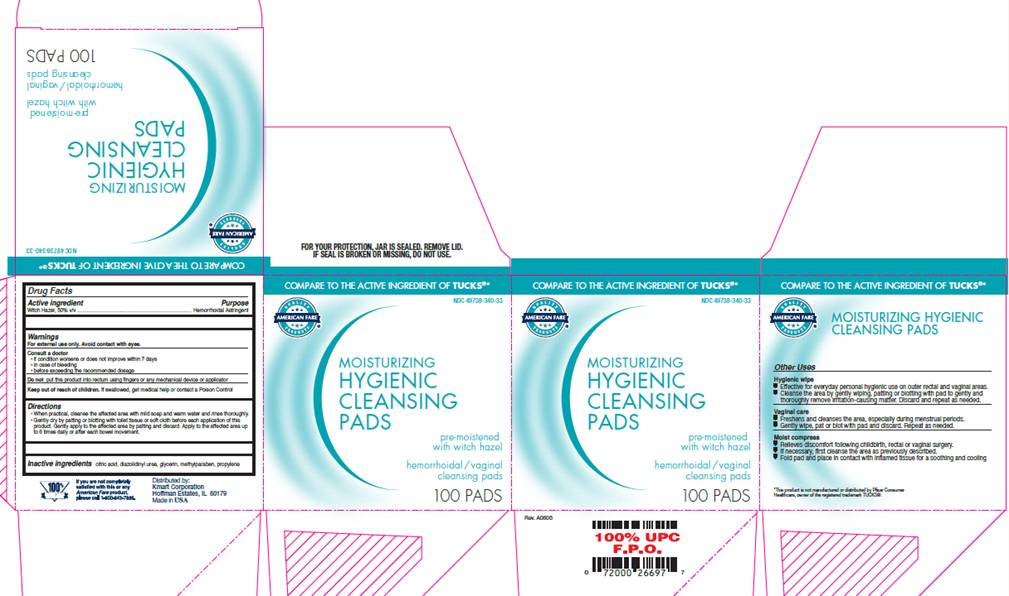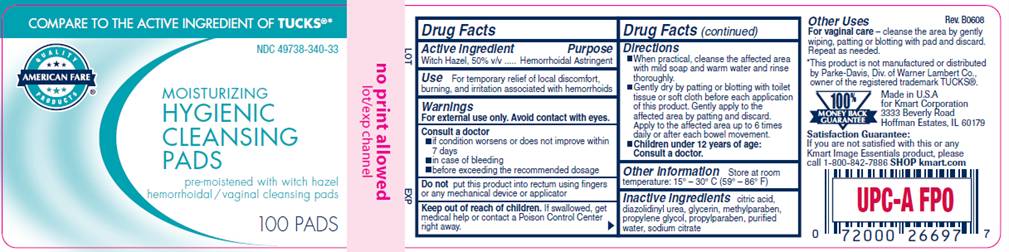 DRUG LABEL: Hygienic Cleansing Pads
NDC: 49738-340 | Form: SOLUTION
Manufacturer: Kmart Corporation
Category: otc | Type: HUMAN OTC DRUG LABEL
Date: 20100416

ACTIVE INGREDIENTS: witch hazel 0.50 mL/1 mL
INACTIVE INGREDIENTS: citric acid monohydrate; diazolidinylurea; glycerin; methylparaben; propylene glycol; propylparaben; sodium citrate; water

DRUG FACTS

ACTIVE INGREDIENT

Witch Hazel 50% v/v

PURPOSE

Hemorrhoidal Astringent

USE

For temporary relief of local discomfort, burning, and irritation associated with hemorrhoids

WARNINGS

For external use only. Avoid contact with eyes.

Consult a doctor

- if condition worsens or does not improve within 7 days
- in case of bleeding
- before exceeding the recommended dosage

Do not

put this product into rectum using fingers or any mechanical device or applicator

Keep out of reach of children

If swallowed, get medical help or contact a Poison Control Center right away.

DIRECTIONS

- When practical, cleanse the affected area with mild soap and warm water and rinse thoroughly.
- Gently dry by patting or blotting with toilet tissue or soft cloth before each application of this product. Gently apply to the affected area by patting and then discard. Apply to the affected area up to 6 times daily or after each bowel movement.
- Children under 12 years of age: consult a doctor.

OTHER INFORMATION

Store at room temperature: 15°- 30° C (59° - 86° F)

OTHER USES

Hygienic wipe

- Effective for everyday personal hygienic use on outer rectal and vaginal areas.
- Cleanse the area by gently wiping, patting or blotting with pad to gently and thoroughly remove irritation-causing matter. Discard and repeat as needed.

Vaginal care

- Freshens and cleanses the area, especially during menstrual periods.
- Gently wipe, pat or blot with pad and discard. Repeat as needed.

Moist compress

- Relieves discomfort following childbirth, rectal or vaginal surgery.
- If necessary, first cleanse the area as previously described.
- Fold pad and place in contact with inflamed tissue for a soothing and cooling

INACTIVE INGREDIENTS

citric acid, diazolidinyl urea, glycerin, methylparaben, propylene glycol, propylparaben, purified water, sodium citrate

PACKAGE INFORMATION

COMPARE TO THE ACTIVE INGREDIENT OF TUCKS®

AMERICAN FARE®

NDC 49738-340-33

MOISTURIZING
HYGIENIC
CLEANSING
PADS

premoistened
with witch hazel

hemorrhoidal / vaginal
cleansing pads

100 PADS